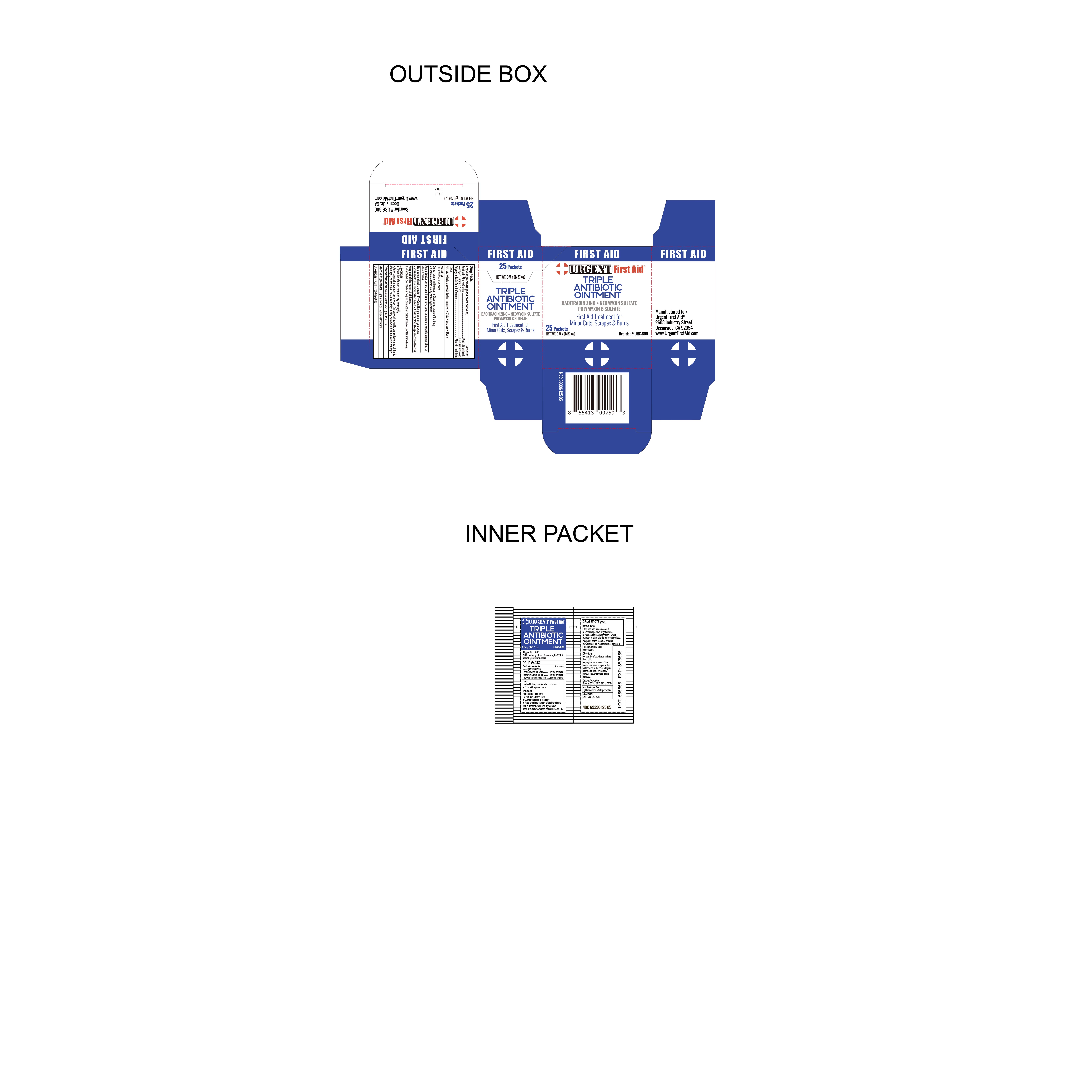 DRUG LABEL: Triple Antibiotic
NDC: 69396-125 | Form: OINTMENT
Manufacturer: TRIFECTA PHARMACEUTICALS USA LLC
Category: otc | Type: HUMAN OTC DRUG LABEL
Date: 20241220

ACTIVE INGREDIENTS: BACITRACIN ZINC 400 [USP'U]/1 g; NEOMYCIN SULFATE 3.5 mg/1 g; POLYMYXIN B SULFATE 5000 [USP'U]/1 g
INACTIVE INGREDIENTS: LIGHT MINERAL OIL; WHITE PETROLATUM

Urgent Triple Antibiotic Ointment

Active ingredients (each gram contains)

Bacitracin zinc 400 units
Neomycin sulfate 3.5 mg
Polymyxin B sulfate 5,000 units

Purpose

First aid antibiotic

Keep out of reach of children. If swallowed, get medical help or contact a Poison Control Center right away.

INDICATIONS AND USAGE

Uses first aid to help prevent infection in minor:● cuts ● scrapes ● burns

Warnings

For external use only.

Ask Doctor before use if you have deep or puncture wounds, animal bites, or serious burns.

Do Not Use

- In the eyes
- Over large areas of the body
- If you are allergic to any of the ingredients

Stop Use and ask a doctor if

- Condition persists or gets worse
- You need to use longer than 1 week
- A rash or other allergic reaction develops

Directions

● clean the affected area and dry thoroughly.

● apply a small amount of this product (an amount equal to the surface area of the tip of a finger) on the area 1 to 3 times daily

● may be covered with a sterile bandage.

Inactive ingredient light Mineral Oil, White Petrolatum

Other information

● store at 20° to 25°C (68° to 77°F)

Questions? Call 1-760-642-2638

Manufactured For

Urgent First Aid®

2603 Industry Street

Oceanside, CA 92054

www.urgentfirstaid.com